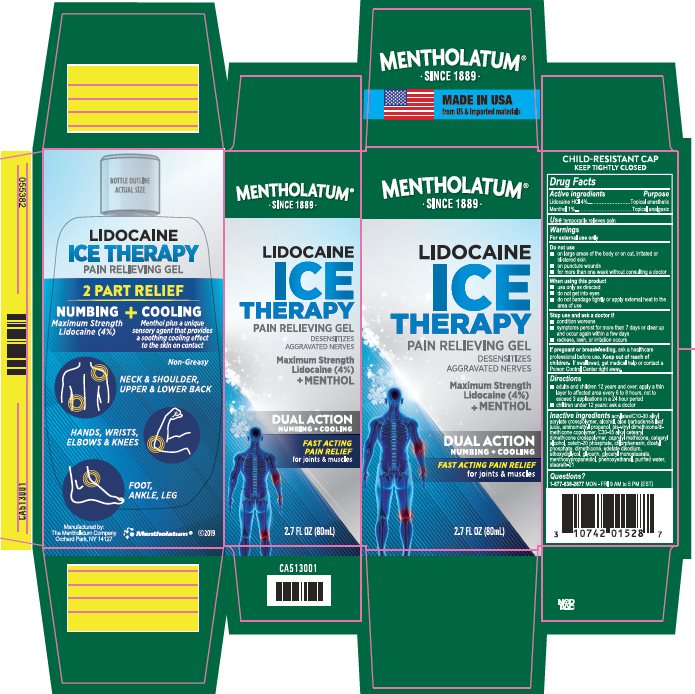 DRUG LABEL: Mentholatum Lidocaine Ice
NDC: 10742-1389 | Form: GEL
Manufacturer: The Mentholatum Company
Category: otc | Type: HUMAN OTC DRUG LABEL
Date: 20241213

ACTIVE INGREDIENTS: LIDOCAINE HYDROCHLORIDE 40 mg/1 mL; MENTHOL, UNSPECIFIED FORM 10 mg/1 mL
INACTIVE INGREDIENTS: CARBOMER INTERPOLYMER TYPE A (ALLYL SUCROSE CROSSLINKED); ALCOHOL; ALOE VERA LEAF; AMINOMETHYLPROPANOL; DIMETHICONE/VINYL DIMETHICONE CROSSPOLYMER (SOFT PARTICLE); CAPRYLYL TRISILOXANE; CETOSTEARYL ALCOHOL; CETETH-20 PHOSPHATE; CHLORPHENESIN; DIHEXADECYL PHOSPHATE; DIMETHICONE; EDETATE DISODIUM; DIETHYLENE GLYCOL MONOETHYL ETHER; GLYCERIN; GLYCERYL MONOSTEARATE; GLYCERIN METHYL ETHER; PHENOXYETHANOL; POLYSORBATE 20; WATER; STEARETH-21

Drug Facts - Mentholatum Lidocaine Ice

Active ingredients

Lidocaine HCl 4%

Menthol 1%

Purpose

Lidocaine HCl - Topical anesthetic

Menthol – Topical analgesic

Uses

temporarily relieves pain

Warnings

For external use only

Do not use

- on large areas of the body or on cut, irritated or blistered skin
- on puncture wounds
- for more than one week without consulting a doctor

When using this product

- use only as directed
- do not get into eyes
- do not bandage tightly or apply external heat to the area of use

Stop use and ask a doctor if

- condition worsens
- symptoms persist for more than 7 days or clear up and occur again within a few days
- redness, rash, or irritation occurs

If pregnant or breast-feeding,

ask a health professional before use.

Keep out of reach of children.

If swallowed, get medical help or contact a Poison Control Center right away.

Directions

- adults and children 12 years and over: apply a thin layer to affected area every 6 to 8 hours, not to exceed 3 applications in a 24 hour period
- children under 12 years: ask a doctor

Inactive ingredients

acrylates/C10-30 alkyl acrylate crosspolymer, alcohol, aloe barbadensis leaf juice, aminomethyl propanol, bis-vinyl dimethicone/dimecthicone copolymer, C30-45 alkyl cetearyl dimethicone crosspolymer, caprylyl methicone, cetearyl alcohol, ceteth-20 phosphate, chlorphenesin, dicetyl phosphate, dimethicone, edetate disodium, ethoxydiglycol, glycerin, glyceryl monostearate, methoxypropanediol, phenoxyethanol, purified water, steareth-21